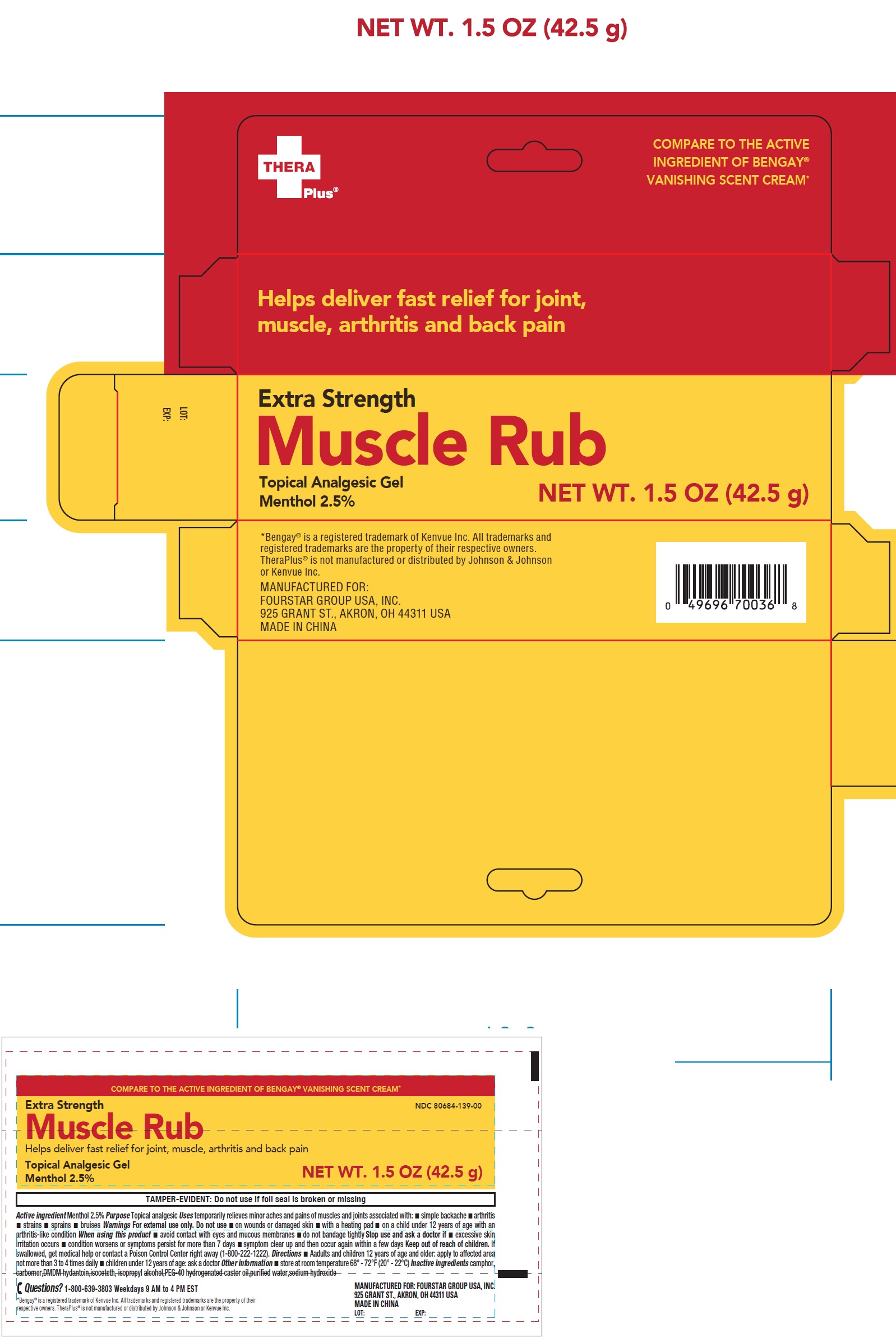 DRUG LABEL: Thera Plus Extra Strength Muscle Rub Topical Analgesic
NDC: 80684-139 | Form: GEL
Manufacturer: FOURSTAR GROUP USA, INC.
Category: otc | Type: HUMAN OTC DRUG LABEL
Date: 20250811

ACTIVE INGREDIENTS: MENTHOL 25 mg/1 g
INACTIVE INGREDIENTS: CARBOMER HOMOPOLYMER, UNSPECIFIED TYPE; CAMPHOR (SYNTHETIC); DMDM HYDANTOIN; ISOPROPYL ALCOHOL; PEG-40 HYDROGENATED CASTOR OIL; WATER; SODIUM HYDROXIDE

Thera Plus Extra Strength Muscle Rub Topical Analgesic Gel

Active ingredients

Menthol 2.5%

Purpose

Topical analgesic

Uses

temporarily relief of minor aches and pains of muscles and joints associated with:

- simple backache
- arthritis
- strains
- sprains
- bruises

Warnings

For external use only.

Do not use

- on wounds or damaged skin
- with a heating pad
- on a child under 12 years of age with an arthritis-like condition

When using this product

- avoid contact with eyes and mucous membranes
- do not bandage tightly

Stop use and ask a doctor if

- excessive skin irritation occurs
- condition worsens or symptoms persist for more than 7 days
- symptoms clear up and then occur again within a few days

Keep out of reach of children.

If swallowed, get medical help or contact a Poison Control Center right away (1-800-222-1222).

Direction

- adults and children 12 years of age and older: apply to affected area not more than 3 to 4 times daily
- children under 12 years of age: ask a doctor

Other information

- store at room temperature 68° - 72°F (20° - 22°C).

Inactive ingredients

camphor,carbomer, DMDM hydantoin, isoceteth, isopropyl alcohol,PEG-40 hydrogenated castor oil,purified water,sodium hydroxide

Questions?

1-800-639-3803Weekdays 9 AM to 4 PM EST